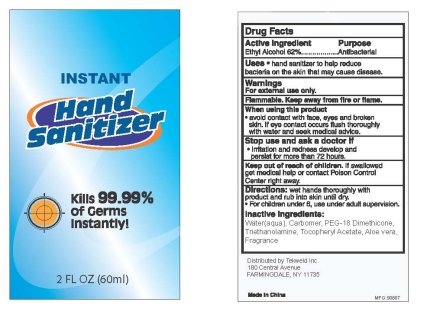 DRUG LABEL: INSTANT HAND SANITIZER
NDC: 31190-400 | Form: GEL
Manufacturer: Shanghai Kejing Cleaning Products Co., Ltd.
Category: otc | Type: HUMAN OTC DRUG LABEL
Date: 20100415

ACTIVE INGREDIENTS: ALCOHOL 62 mL/100 mL
INACTIVE INGREDIENTS: WATER; TROLAMINE

INSTANT HAND SANITIZER 60mL

Active Ingredient Purpose

Ethyl Alcohol 62%...................Antibacterial

PURPOSE

Uses: hand sanitizer to help reduce bacteria on the skin that may cause disease.

Warnings
For external use only.
Flammable, keep away from fire or flame.

When using this product

avoid contact with face, eyes and broken skin. If eye contact occurs flush thoroughly with water and seek medical advice.

Stop use and ask a doctor if; irritation and redness develop and persist for more than 72 hours.

Keep out of reach of children; If swallowed get medical help or contact Poison Control Center right away.

DOSAGE AND ADMINISTRATION

Directions: wet hands thoroughly with product and rub into skin until dry.
For children under 6, use under adult supervision.

INACTIVE INGREDIENT

Inactive Ingredients: Water(aqua), Carbomer, PEG-18 Dimethicone, Triethanolamine, Tocopheryl Acetate, Aloe vera, Fragrance

DESCRIPTION

Distributed by Tekweld Inc.
180 Central Avenue
FARMINGDALE, NY 11735

Made in China MFG: 90807

PACKAGE LABEL

INSTANT HAND SANITIZER

Kills 99/99 % of Germs Instantly!

2 FL OZ (60ml)